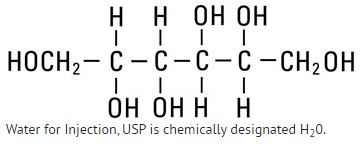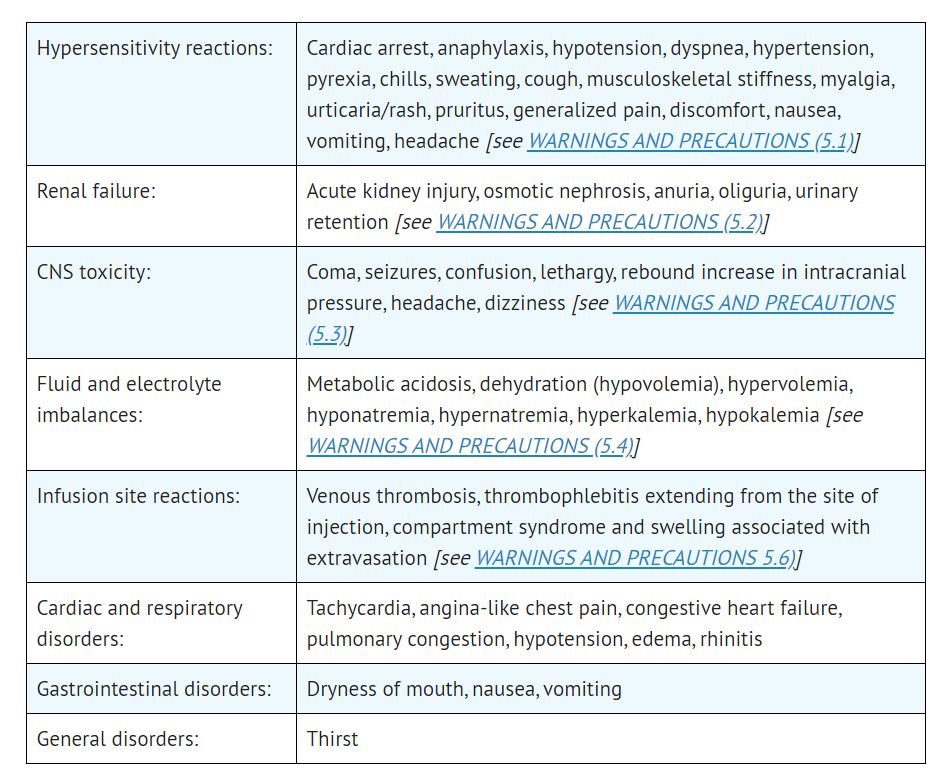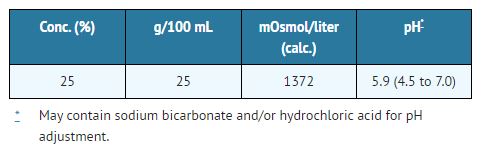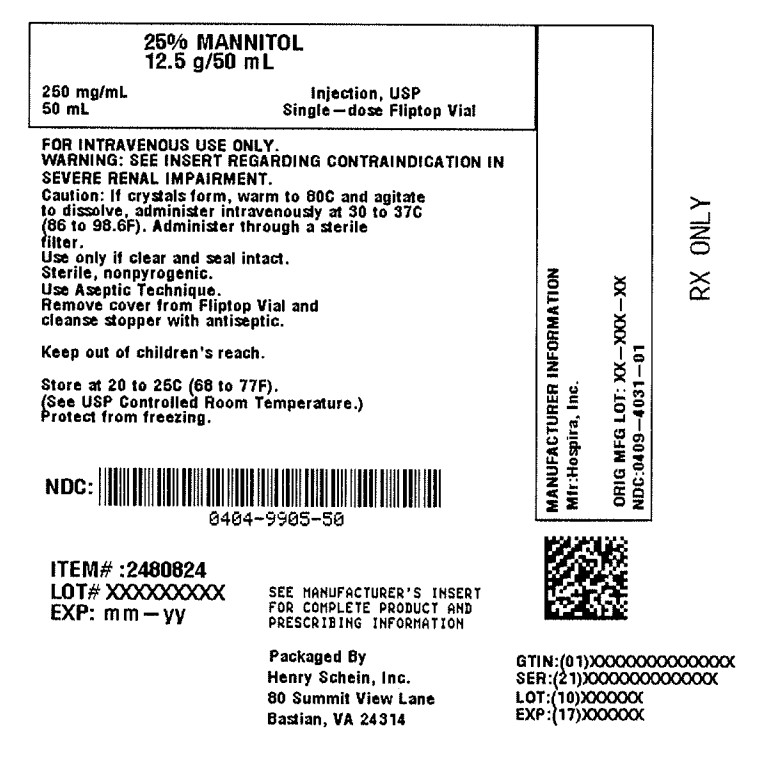 DRUG LABEL: Mannitol
NDC: 0404-9905 | Form: INJECTION, SOLUTION
Manufacturer: Henry Schein, Inc.
Category: prescription | Type: HUMAN PRESCRIPTION DRUG LABEL
Date: 20250520

ACTIVE INGREDIENTS: Mannitol 12.5 g/50 mL

HIGHLIGHTS OF PRESCRIBING INFORMATION

HIGHLIGHTSOF PRESCRIBING INFORMATIONThese highlights do not include all the information needed to use MANNITOL INJECTION safely and effectively. See full prescribing information for MANNITOL INJECTION.MANNITOL injection, for intravenous use
Initial U.S. Approval: 1964

Recent Major Changes

Indications and Usage (removed, revised) (1) | 03/2020
Contraindications (4) | 03/2020
Warnings and Precautions (5.1, 5.2, 5.3, 5.4, 5.5, 5.6, 5.7) | 03/2020

1 INDICATIONS AND USAGE

Mannitol Injection is an osmotic diuretic, indicated for the reduction of:

- intracranial pressure and treatment of cerebral edema. (1)
- elevated intraocular pressure. (1)

2 DOSAGE AND ADMINISTRATION

Administration Instructions (2.1):

For intravenous infusion, preferably through a central venous catheter.
Prior to administration, evaluate renal, cardiac and pulmonary status and correct fluid and electrolyte imbalances.
Recommended Dosage (2.2):

The dosage, concentration and rate of administration depend on the age, weight and condition of the patient, including fluid requirement, urinary output and concomitant therapy.
Reduction of Intracranial Pressure and Treatment of Cerebral Edema: 0.25 g/kg administered every 6 to 8 hours as an intravenous infusion over at least 30 minutes.
Reduction of Intraocular Pressure: 1.5 to 2 g/kg administered as a single dose intravenously over at least 30 minutes. Administer 60 to 90 minutes before surgery to achieve maximal effect.

3 DOSAGE FORMS AND STRENGTHS

Mannitol Injection 25%, USP: 12.5 g/50 mL (0.25 g/mL) in a single-dose vial (3)

4 CONTRAINDICATIONS

- Known hypersensitivity to mannitol. (4, 5.1)
- Anuria. (4, 5.2)
- Severe hypovolemia. (4, 5.4)
- Pre-existing severe pulmonary vascular congestion or pulmonary edema. (4, 5.5)
- Active intracranial bleeding except during craniotomy. (4)

5 WARNINGS

- Hypersensitivity Reactions, Including Anaphylaxis: Stop infusion immediately if hypersensitivity reactions develop. (5.1)
- Renal Complications Including Renal Failure: Risk factors include pre-existing renal disease, conditions that put patients at risk for renal failure and concomitant use of nephrotoxic drugs or other diuretics. Avoid use of nephrotoxic drugs. Discontinue Mannitol Injection if renal function worsens. (5.2, 8.6)
- Central Nervous System (CNS) Toxicity: Confusion, lethargy, and coma may occur during or after infusion. Concomitant neurotoxic drugs may potentiate toxicity. Avoid use of neurotoxic drugs. Discontinue Mannitol Injection if CNS toxicity develops. (5.3)
- Fluid and Electrolyte Imbalances, Hyperosmolarity: Hypervolemia may exacerbate congestive heart failure; hyponatremia can lead to encephalopathy; hypo/hyperkalemia can result in cardiac adverse reactions in sensitive patients. Discontinue Mannitol Injection if fluid and/or electrolyte imbalances occur. (5.4)
- Monitoring/Laboratory Tests: Monitor fluid and electrolytes, serum osmolarity and renal, cardiac, and pulmonary function. Discontinue if toxicity develops. (5.5)
- Infusion Site Reactions: May cause irritation and inflammation, as well as severe reactions (compartment syndrome) when associated with extravasation. (5.6)
- Interference with Laboratory Tests: High concentrations of mannitol may cause false low results of inorganic phosphorus blood concentrations. Mannitol may produce false positive results for blood ethylene glycol. (5.7, 7.6)

6 ADVERSE REACTIONS

Most common adverse reactions are hypersensitivity reactions, renal failure, CNS toxicity, hypo/hypervolemia, hypo/hypernatremia, hypo/hyperkalemia, and infusion site reactions. (6)

To report SUSPECTED ADVERSE REACTIONS, contact Hospira, Inc. at 1-800-441-4100 or FDA at 1-800-FDA-1088 or www.fda.gov/medwatch.

7 DRUG INTERACTIONS

- Nephrotoxic Drugs and Diuretics: May increase the risk of renal failure; avoid concomitant use. (7.1, 7.2)
- Neurotoxic Drugs: May potentiate CNS toxicity of mannitol; avoid concomitant use. (7.3)
- Drugs Affected by Electrolyte Imbalances: May result in cardiac adverse reactions; monitor serum electrolytes and discontinue Mannitol Injection if cardiac status worsens. (7.4)
- Renally Eliminated Drugs: Concomitant use may decrease the effectiveness of agents that undergo significant renal elimination. However, concomitant use of mannitol and lithium may increase risk of lithium toxicity. If concomitant use is necessary, frequently monitor lithium concentrations and for signs of toxicity. (7.5)

See 17 for PATIENT COUNSELING INFORMATION.

Revised: 3/2020

FULL PRESCRIBING INFORMATION

These highlights do not include all the information needed to use MANNITOL INJECTION safely and effectively. See full prescribing information for MANNITOL INJECTION.

MANNITOL injection, for intravenous use
Initial U.S. Approval: 1964

1 INDICATIONS AND USAGE

Mannitol Injection is indicated for the reduction of:

- intracranial pressure and treatment of cerebral edema.
- elevated intraocular pressure.

2 DOSAGE AND ADMINISTRATION

2.1 Important Preparation and Administration Instructions

Mannitol Injection is for intravenous infusion preferably through a central venous catheter [see WARNINGS AND PRECAUTIONS (5.6), DESCRIPTION (11)].
Prior to the administration of Mannitol Injection, evaluate renal, cardiac, and pulmonary status of the patient and correct fluid and electrolyte imbalances [see DOSAGE AND ADMINISTRATION (2.2)].
Do not administer Mannitol Injection simultaneously with blood products or through the same administration set because of the possibility of pseduoagglutination or hemolysis. If it is essential that blood be given simultaneously, at least 20 mEq of sodium chloride should be added to each liter of mannitol solution to avoid pseudoagglutination.
Do not transfer Mannitol Injection into polyvinylchloride (PVC) bags; a white flocculent precipitate may form from contact with PVC surfaces.
Administer Mannitol Injection using an administration set with a filter to ensure against infusion of mannitol crystals.
Preparation

Visually inspect the container before preparation and again before administration. Do not administer unless solution is clear, the container undamaged, and the fliptop vial seal intact.
Crystals may form in Mannitol Injection, especially if the solution is exposed to low temperatures. If crystallization occurs, warm the vial in water at 80°C and periodically shake vigorously to dissolve the crystals. Mannitol Injection may be autoclaved at 121°C for 20 minutes at 15 psi. Cool to body temperature or less before administering. Re-inspect Mannitol Injection for crystals prior to administration. Discard the solution if all the crystals cannot be dissolved.
Remove cover from fliptop vial and cleanse stopper with antiseptic before use.
Additives may be incompatible. Consult with pharmacist, if available.
For single use only; discard unused portion.
2.2 Recommended Dosage
Prior to administration of Mannitol Injection, evaluate renal, cardiac, and pulmonary status of the patient and correct fluid and electrolyte imbalances.

The total dosage, concentration, and rate of administration depend on the age, weight, and condition of the patient being treated, including fluid requirement, electrolyte balance, serum osmolality, urinary output, and concomitant therapy.

The following outline of administration and dosage is only a general guide to therapy.

Reduction of Intracranial Pressure and Treatment of Cerebral Edema

Usually a maximum reduction in intracranial pressure can be achieved with a dose of 0.25 g/kg administered as an intravenous infusion over at least 30 minutes, which may be repeated every six to eight hours. During and following infusion of Mannitol Injection, monitor fluid and electrolytes, serum osmolarity, and renal, cardiac, and pulmonary function. Discontinue Mannitol Injection if renal, cardiac, or pulmonary status worsens or CNS toxicity develops [see WARNINGS AND PRECAUTIONS (5.2, 5.3, 5.4, 5.5)].

Reduction of Intraocular Pressure

The recommended dosage is 1.5 to 2 g/kg as a single dose administered as an intravenous infusion over at least 30 minutes. When used preoperatively, administer Mannitol Injection 60 to 90 minutes before surgery to achieve maximal reduction of intraocular pressure before operation.

3 DOSAGE FORMS AND STRENGTHS

Mannitol Injection 25%, USP: 12.5 g/50 mL (0.25 g/mL) of mannitol as a clear and colorless solution in a single-dose vial.

4 CONTRAINDICATIONS

Mannitol Injection is contraindicated in patients with:

- Known hypersensitivity to mannitol [see WARNINGS AND PRECAUTIONS (5.1)].
- Anuria [see WARNINGS AND PRECAUTIONS (5.2)].
- Severe hypovolemia [see WARNINGS AND PRECAUTIONS (5.4)].
- Pre-existing severe pulmonary vascular congestion or pulmonary edema [see WARNINGS AND PRECAUTIONS (5.5)].
- Active intracranial bleeding except during craniotomy.

5 WARNINGS

5.1 Hypersensitivity Reactions
Serious hypersensitivity reactions, including anaphylaxis, hypotension, and dyspnea resulting in cardiac arrest and death have been reported with Mannitol Injection [see ADVERSE REACTIONS (6)]. Stop the infusion immediately if signs or symptoms of a suspected hypersensitivity reaction develop. Initiate appropriate therapeutic countermeasures as clinically indicated.

5.2 Renal Complications Including Renal Failure
Renal complications, including irreversible renal failure, have been reported in patients receiving mannitol.

Reversible, oliguric acute kidney injury has occurred in patients with normal pretreatment renal function who received large intravenous doses of mannitol. Although the osmotic nephrosis associated with mannitol administration is in principle reversible, osmotic nephrosis in general is known to potentially proceed chronic or even end-stage renal failure. Monitor renal function closely, including signs of urine output reduction, during mannitol injection.

Patients with pre-existing renal disease, patients with conditions that put them at risk for renal failure, or those receiving potentially nephrotoxic drugs or other diuretics, are at increased risk for renal failure following administration of Mannitol Injection. Avoid concomitant administration of nephrotoxic drugs (e.g., aminoglycosides) or other diuretics with Mannitol Injection, if possible [see DRUG INTERACTIONS (7)].

Patients with oliguric acute kidney injury who subsequently develop anuria while receiving mannitol are at risk of congestive heart failure, pulmonary edema, hypertensive crisis, coma, and death.

During and following infusion of Mannitol Injection for the reduction in intracranial pressure, monitor the patient clinically and laboratory tests for changes in fluid and electrolyte status. Discontinue Mannitol Injection if renal function worsens [see WARNINGS AND PRECAUTIONS (5.5)].

5.3 Central Nervous System (CNS) Toxicity
CNS toxicity manifested by, e.g., confusion, lethargy, coma, has been reported in patients treated with mannitol, some resulting in death, in particular in the presence of impaired renal function CNS toxicity may result from high serum mannitol concentrations, serum hyperosmolarity resulting in intracellular dehydration within CNS, hyponatremia or other disturbances of electrolyte and acid/base balance secondary to mannitol administration [see WARNINGS AND PRECAUTIONS (5.4)].

At high concentrations, mannitol may cross the blood brain barrier and interfere with the ability of the brain to maintain the pH of the cerebrospinal fluid especially in the presence of acidosis.

In patients with pre-existing compromise of the blood brain barrier, the risk of increasing cerebral edema (general and focal) associated with repeated or continued use of Mannitol Injection must be individually weighed against the expected benefits.

A rebound increase of intracranial pressure may occur several hours after the infusion. Patients with a compromised blood brain barrier are at increased risk.

Concomitant administration of neurotoxic drugs (e.g., aminoglycosides) with Mannitol Injection may potentiate neurotoxicity. Avoid concomitant use of neurotoxic drugs, if possible [see DRUG INTERACTIONS (7.3)].

During and following infusion of Mannitol Injection for the reduction in intracranial pressure, monitor the patient clinically and laboratory tests for changes in fluid and electrolyte status. Discontinue Mannitol Injection if CNS toxicity develops [see WARNINGS AND PRECAUTIONS (5.5)].

5.4 Fluid and Electrolyte Imbalances, Hyperosmolarity
Depending on dosage and duration, administration of Mannitol Injection may result in hypervolemia leading to or exacerbating existing congestive heart failure. Accumulation of mannitol due to insufficient renal excretion increases the risk of hypervolemia. Mannitol-induced osmotic diuresis may cause or worsen dehydration/hypovolemia and hemoconcentration. Administration of Mannitol Injection may also cause hyperosmolarity [see DESCRIPTION (11)].

Depending on dosage and duration of administration, electrolyte and acid/base imbalances may also result from transcellular shifts in water and electrolytes, osmotic diuresis, and/or other mechanisms. Such imbalances may be severe and potentially fatal.

Imbalances that may result from administration of Mannitol Injection include:

- Hypernatremia, dehydration, and hemoconcentration
- Hyponatremia, which can lead to headache, nausea, seizures, lethargy, coma, cerebral edema, and death. Acute symptomatic hyponatremic encephalopathy is considered a medical emergency.
- Hypo/hyperkalemia. The development of electrolyte imbalances (e.g., hyperkalemia, hypokalemia) associated with mannitol administration may result in cardiac adverse reactions in patients receiving drugs that are sensitive to such imbalances (e.g., digoxin, agents that may cause QT prolongation, neuromuscular blocking agents) [see DRUG INTERACTIONS (7.4)].
- Other electrolyte disturbances
- Metabolic acidosis/alkalosis
- Pediatric patients less than two years of age, particularly preterm and term neonates, may be at higher risk for fluid and electrolyte abnormalities following administration of Mannitol Injection due to decreased glomerular filtration rate and limited ability to concentrate urine [see USE IN SPECIFIC POPULATIONS (8.4)].
- During and following infusion of Mannitol Injection for the reduction in intracranial pressure, monitor fluid and electrolyte status and discontinue Mannitol Injection if imbalances occur [see WARNINGS AND PRECAUTIONS (5.5)].

5.5 Monitoring/Laboratory Tests
During and following infusion of Mannitol Injection for the reduction in intracranial pressure, monitor:

- serum osmolarity, serum electrolytes (including sodium, potassium, calcium and phosphate) and acid/base balance,
- the osmol gap
- signs of hypo- or hypervolemia, including urine output
- renal, cardiac, and pulmonary function
- intracranial pressure
- Discontinue Mannitol Injection if renal, cardiac, or pulmonary status worsens or CNS toxicity develops [see CONTRAINDICATIONS (4)].

5.6 Infusion Site Reactions
The infusion of hypertonic solutions through a peripheral vein, including Mannitol Injection, may result in peripheral venous irritation, including phlebitis. Other severe infusion site reactions, such as compartment syndrome and swelling associated with extravasation, can occur with administration of Mannitol Injection [see ADVERSE REACTIONS (6)]. Mannitol Injection is preferably administered through a central venous catheter [see DOSAGE AND ADMINISTRATION (2.1)].

5.7 Interference with Laboratory Tests
High concentrations of mannitol can cause false low results for inorganic phosphorus blood concentrations [see DRUG INTERACTIONS (7.6)].

Mannitol may produce false positive results in tests for blood ethylene glycol concentrations [see DRUG INTERACTIONS (7.6)].

6 ADVERSE REACTIONS

The following adverse reactions associated with the use mannitol were identified in clinical studies or postmarketing reports. Because some of these reactions were reported voluntarily from a population of uncertain size, it is not always possible to reliably estimate their frequency or establish a causal relationship to drug exposure.

7 DRUG INTERACTIONS

7.1 Nephrotoxic Drugs
Concomitant administration of nephrotoxic drugs (e.g., cyclosporine, aminoglycosides) increases the risk of renal failure following administration of mannitol. Avoid use of nephrotoxic drugs with Mannitol Injection, if possible [see WARNINGS AND PRECAUTIONS (5.2)].

7.2 Diuretics
Concomitant administration of other diuretics may potentiate the renal toxicity of mannitol. Avoid concomitant administration of other diuretics with Mannitol Injection, if possible [see WARNINGS AND PRECAUTIONS (5.2)].

7.3 Neurotoxic Drugs
Concomitant administration of systemic neurotoxic drugs (e.g., aminoglycosides) with Mannitol Injection may potentiate the CNS toxicity of mannitol. Avoid use of systemic neurotoxic drugs with Mannitol Injection, if possible [see WARNINGS AND PRECAUTIONS (5.3)].

7.4 Drugs Affected by Electrolyte Imbalances
The development of electrolyte imbalances (e.g., hyperkalemia, hypokalemia) associated with mannitol administration may result in cardiac adverse reactions in patients receiving drugs that are sensitive to such imbalances (e.g., digoxin, drugs that prolong the QT interval, neuromuscular blocking agents) [see WARNINGS AND PRECAUTIONS (5.4)]. During and following infusion of Mannitol Injection, monitor serum electrolytes and discontinue Mannitol Injection if cardiac status worsens [see WARNINGS AND PRECAUTIONS (5.5)].

7.5 Renally Eliminated Drugs
Mannitol therapy may increase the elimination, and decrease the effectiveness of treatment with, drugs that undergo significant renal elimination. Concomitant administration of mannitol with lithium may initially increase the elimination of lithium but may also increase the risk of lithium toxicity if patients develop hypovolemia or renal impairment. In patients receiving lithium, consider holding lithium doses during treatment with Mannitol Injection. In patients requiring concomitant administration of lithium and Mannitol Injection, frequently monitor serum lithium concentrations and for signs of lithium toxicity.

7.6 Interference with Laboratory Tests
High concentrations of mannitol can cause false low results for inorganic phosphorus blood concentrations when an assay based on the conversion of phosphate (orthophosphate) to the phosphomolybdate complex is used.

Mannitol may produce false positive results in tests for blood ethylene glycol concentrations in which mannitol is initially oxidized to an aldehyde.

8 USE IN SPECIFIC pOPULATIONS

8.1 Pregnancy
Risk Summary

The available case report data with mannitol over decades of use have not identified a drug-associated risk of major birth defects, miscarriage or adverse maternal or fetal outcomes. Mannitol crosses the placenta and may cause fluid shifts that could potentially result in adverse effects in the fetus (see DATA).No adverse developmental effects from mannitol were reported in published animal studies; however, fluid shifts occurred in fetal ewes in response to maternal infusion of mannitol.

The estimated background risk of major birth defects and miscarriage for the indicated population is unknown. All pregnancies have a background risk of birth defect, loss, or other adverse outcomes. In the U.S. general population, the estimated background risk of major birth defects and miscarriage in clinically recognized pregnancies is 2 to 4% and 15 to 20%, respectively.

Data

Human Data

Published literature reports the presence of mannitol in amniotic fluid when mannitol is administered to pregnant women during the third trimester of pregnancy.

8.2 Lactation
Risk Summary

There are no data on the presence of mannitol in either human or animal milk, the effects on the breastfed infant, or the effects on milk production. The developmental and health benefits of breastfeeding should be considered along with the mother's clinical need for Mannitol Injection and any potential adverse effects on the breastfed child from Mannitol Injection or from the underlying maternal condition.

8.4 Pediatric Use
Mannitol Injection is approved for use in the pediatric population for the reduction of intracranial and intraocular pressure. Studies have not defined the optimal dose of Mannitol Injection in the pediatric population. The safety profile for mannitol use in pediatric patients is similar to adults at dosages described in labeling. However, pediatric patients less than two years of age, particularly preterm and term neonates, may be at higher risk for fluid and electrolyte abnormalities following administration of Mannitol Injection due to decreased glomerular filtration rate and limited ability to concentrate urine [see WARNINGS AND PRECAUTIONS (5.4)].

8.5 Geriatric Use
Mannitol is known to be substantially excreted by the kidney, and the risk of adverse reactions to this drug may be greater in elderly patients with impaired renal function. Evaluate the renal, cardiac and pulmonary status of the patient and correct fluid and electrolyte imbalances prior to administration of Mannitol Injection [see WARNINGS AND PRECAUTIONS (5.2, 5.3, 5.4, 5.5)].

8.6 Renal Impairment
Patients with pre-existing renal disease, patients with conditions that put them at high risk for renal failure, or those receiving potentially nephrotoxic drugs or other diuretics, are at increased risk of renal failure with administration of mannitol. Evaluate the renal, cardiac, and pulmonary status of the patient and correct fluid and electrolyte imbalances prior to administration of Mannitol Injection [see WARNINGS AND PRECAUTIONS (5.2, 5.3, 5.4, 5.5)].

9 OVERDOSAGE

Signs and symptoms of overdose with Mannitol Injection include renal failure and acute kidney injury, hypo/hypervolemia, hyperosmolarity and electrolyte imbalances, CNS toxicity (e.g., coma, seizures), some of which can be fatal [see WARNINGS AND PRECAUTIONS (5.2, 5.3, 5.4)].

Management of overdosage with Mannitol Injection is symptomatic and supportive. Discontinue the infusion and institute appropriate corrective measures with particular attention to renal, cardiac, and pulmonary systems. Correct fluid and electrolyte imbalances.

Mannitol Injection is dialyzable (hemodialysis and peritoneal dialysis), hemodialysis may increase mannitol elimination.

11 DESCRIPTION

Mannitol Injection, USP is a sterile, nonpyrogenic solution of mannitol in water for injection available in a fliptop vial for intravenous administration as an osmotic diuretic.

The content and characteristics are as follows:

The solution contains no bacteriostat, antimicrobial agent, or added buffer (except for pH adjustment) and is intended only as a single-dose injection.

Mannitol, USP is chemically designated D-mannitol (C6H14O6), a white crystalline powder or free-flowing granules freely soluble in water. It has the following structural formula:

12 CLINICAL PHARMACOLOGY

12.1 Mechanism of Action
Mannitol, when administered intravenously, exerts its osmotic diuretic effect as a solute of relatively small molecular size largely confined to the extracellular space. Mannitol hinders tubular reabsorption of water and enhances excretion of sodium and chloride by elevating the osmolarity of the glomerular filtrate.

This increase in extracellular osmolarity affected by the intravenous administration of mannitol will induce the movement of intracellular water to the extracellular and vascular spaces. This action underlies the role of mannitol in reducing intracranial pressure, intracranial edema, and intraocular pressure.

12.3 Pharmacokinetics
Distribution

Mannitol distributes largely to the extracellular space within 20 to 40 minutes after intravenous administration. The volume of distribution of mannitol is approximately 17 L in adults.

Elimination

In subjects with normal renal function, the total clearance is 87 to 109 mL/minute. The elimination half-life of mannitol is 0.5 to 2.5 hours

Metabolism

Only a relatively small amount of the mannitol dose is metabolized after intravenous administration to healthy subjects.

Excretion

Mannitol is eliminated primarily via the kidneys in unchanged form. Mannitol is filtered by the glomeruli, exhibits less than 10% of tubular reabsorption, and is not secreted by tubular cells. Following intravenous administration, approximately 80% of an administered dose of mannitol is estimated to be excreted in the urine in 3 hours with lesser amounts thereafter.

Specific Populations

Patients with Renal Impairment

In patients with renal impairment, the elimination half-life of mannitol is prolonged. In a published study, in patients with renal impairment including acute renal failure and end stage renal failure, the elimination half-life of mannitol was estimated at about 36 hours, based on serum osmolarity. In patients with renal impairment on dialysis, the elimination half-life of mannitol was reduced to 6 and 21 hours during hemodialysis and peritoneal dialysis, respectively [see USE IN SPECIFIC POPULATIONS (8.6), OVERDOSAGE (10)].

16 HOW SUPPLIED/ STORAGE AND HANDLING

Mannitol Injection 25%, USP is available as 12.5 g/50 mL (0.25 g/mL) of mannitol in a single-dose vial. Supplied as a tray of 25 vials (NDC 0409-4031-01).

Store at 20 to 25°C (68 to 77°F). [See USP Controlled Room Temperature.] Protect from freezing.

Product repackaged by: Henry Schein, Inc., Bastian, VA 24314
From Original Manufacturer/Distributor's NDC and Unit of Sale | To Henry Schein Repackaged Product NDC and Unit of Sale | Total Strength/Total Volume (Concentration) per unit
NDC 0409-4031-01 Supplied in a tray of 25 | NDC 0404-9905-50 1 single dose vial in a bag (Vial bears NDC 0409-4031-16) | 25% 12.5 mg/50mL (0.25 mg/mL)

17 PATIENT COUNSELING INFORMATION

Inform patients or caregivers of the following risks of Mannitol Injection:

Hypersensitivity Reactions [see WARNINGS AND PRECAUTIONS (5.1)]
Renal Complications Including Renal Failure [see WARNINGS AND PRECAUTIONS (5.2)].
CNS Toxicity [see WARNINGS AND PRECAUTIONS (5.3)]
Fluid and Electrolyte Imbalances, Hyperosmolarity [see WARNINGS AND PRECAUTIONS (5.4)]
Infusion Site Reactions [see WARNINGS AND PRECAUTIONS (5.6)]

Distributed by Hospira, Inc., Lake Forest, IL 60045 USA

LAB-1227-2.0